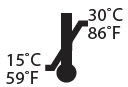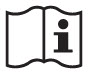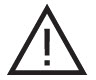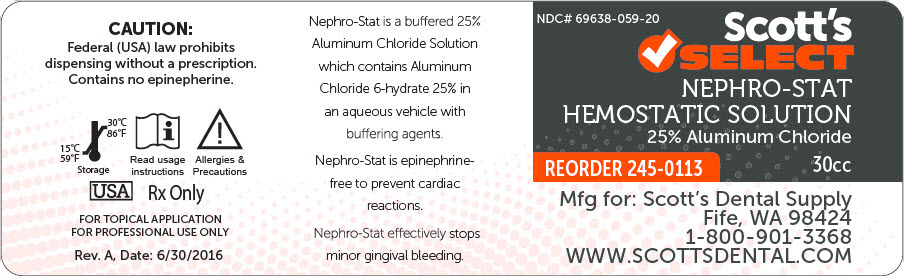 DRUG LABEL: Scotts Select NEPHRO-stat
NDC: 69638-059 | Form: Solution
Manufacturer: Scott's Dental Supply LLC
Category: prescription | Type: HUMAN PRESCRIPTION DRUG LABEL
Date: 20200306

ACTIVE INGREDIENTS: ALUMINUM CHLORIDE 7500 mg/30 mL
INACTIVE INGREDIENTS: WATER; POTASSIUM CHLORIDE; PROPYLENE GLYCOL; BENZYL ALCOHOL

Scott's SELECT
NEPHRO-STAT HEMOSTATIC SOLUTION

NDC# 69638-059-20

25% Aluminum Chloride

30cc

INSTRUCTIONS FOR USE

Drug Facts

Active Ingredient | Purpose
25% Aluminum Chloride | Astringent

USES

Nephro-Stat is a topical astringent solution of Aluminum Chloride. Gingival retraction can be achieved using a plain gingival retraction cord moistened with Nephro-Stat. Stops gingival bleeding fast. If you should inadvertently damage the gingival margin during tooth preparation or while placing a strip, a band or a cervical matrix, moisten the area with Nephro-Stat which will control and stop bleeding quickly.

Nephro-Stat contains no epinephrine. The use of vasoconstrictors for gingival retractions and bleeding is potentially dangerous and should be avoided.

A plain gingival retraction cord can be dipped in Nephro-Stat solution and then placed into the gingival sulcus for its hemostatic action.

WARNINGS

- Discontinue use if irritation appears.
  For topical application only.
- Avoid eye contact.
- Do not use in patients with a known history of hypersensitivity to aluminum chloride.
- For professional use only.
- Federal law restricts the product to sale or use on the order of a dentist.

DIRECTIONS FOR USE

- Soak a cotton tipped applicator with Nephro-Stat.
- Apply to bleeding area with pressure until bleeding is stopped. Should a small dark coagulation appear, flush it away with water.
  This will have no effect on hemostatic action.
- Remove the impregnated cord from sulcus.
- Flush with water and air dry until bleeding is no longer present.

OTHER INFORMATION

Store at 59° – 86°F (15° – 30°C).

Protect from freezing.

INACTIVE INGREDIENTS

Benzyl Alcohol, Distilled Water, Potassium Chloride, Propylene Glycol

CAUTION

Federal (USA) law prohibits dispensing without a prescription.

Contains no epinepherine.

Storage

Read usage instructions

Allergies & Precautions

USA
Rx Only

FOR TOPICAL APPLICATION

FOR PROFESSIONAL USE ONLY

Rev. A, Date: 6/30/2016

REORDERING

To reorder Scott's Select Nephro-Stat please call customer sercive at 1-800-901-3368 or by visitng WWW. SCOTTSDENTAL.COM using reorder number 245-0113.

FEATURES

- Nephro-Stat is a buffered 25% Aluminum Chloride Solution which contains Aluminum Chloride 6-hydrate 25% in an aqueous vehicle with buffering agents.
- Nephro-Stat is epinephrine-free to prevent cardiac reactions.
- Nephro-Stat effectively stops minor gingival bleeding.
- It is recommended to arrest bleeding during crown preparations, before impression taking, for minor surgery, curettage, gingivectomies, and deep scaling.
- Nephro-Stat is easily absorbed by retraction cords.

Mfg for: Scott's Dental Supply
Fife, WA 98424
1-800-901-3368
WWW.SCOTTSDENTAL.COM

PRINCIPAL DISPLAY PANEL - 30 cc Bottle Label

NDC# 69638-059-20

Scott's
SELECT
NEPHRO-STAT
HEMOSTATIC SOLUTION
25% Aluminum Chloride

REORDER 245-0113

30cc

Mfg for: Scott's Dental Supply
Fife, WA 98424
1-800-901-3368
WWW.SCOTTSDENTAL.COM